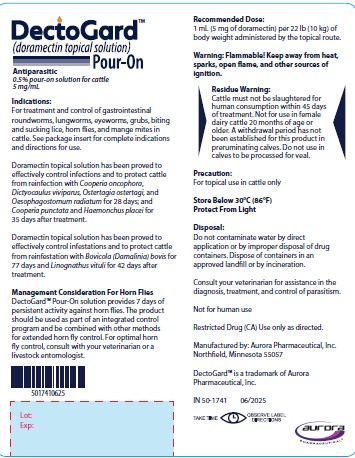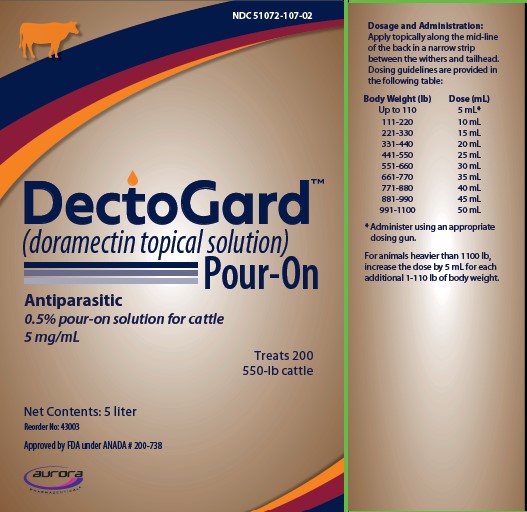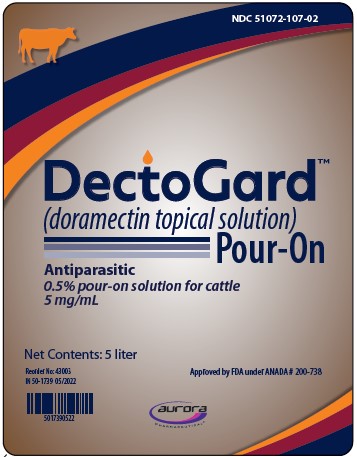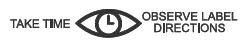 DRUG LABEL: DectoGard
NDC: 51072-107 | Form: SOLUTION
Manufacturer: Aurora Pharmaceutical, Inc.
Category: animal | Type: OTC ANIMAL DRUG LABEL
Date: 20260216

ACTIVE INGREDIENTS: DORAMECTIN 5 mg/1 mL

DectoGardTM

(doramectin topical solution) Pour-On

Antiparasitic

0.5% pour-on solution for cattle
5 mg/mL

PRODUCT DESCRIPTION:

DectoGard Pour-On solution is a ready-to-use, systemically active, clear, light blue solution containing 0.5% w/v doramectin (5 mg/mL). It is formulated to deliver the recommended dosage of 500 mcg/kg (227 mcg/lb) of body weight when given by topical administration at the rate of 1 mL/22 lb (10 kg) of body weight.

PRODUCT CHARACTERISTICS:

DectoGard Pour-On solution is a highly active, broad-spectrum parasiticide for topical administration to cattle. It contains doramectin, a novel fermentation-derived macrocyclic lactone discovered by Pfizer Inc. Doramectin is isolated from fermentations of selected strains derived from the soil organism Streptomyces avermitilis.

A primary mode of action of macrocyclic lactones is to modulate chloride ion channel activity in the nervous system of nematodes and arthropods. Macrocyclic lactones bind to receptors that increase membrane permeability to chloride ions. This inhibits the electrical activity of nerve cells in nematodes and muscle cells in arthropods and causes paralysis and death of the parasites. In mammals, the neuronal receptors to which macrocyclic lactones bind are localized within the central nervous system (CNS), a site reached by only negligible concentrations of doramectin.

One dose of DectoGard Pour-On solution effectively treats and controls a wide range of roundworm and arthropod parasites that impair the health and productivity of cattle.

Studies have demonstrated the safety margin of doramectin. In USA trials, no toxic signs were seen in cattle given up to 25 times the recommended dose of doramectin injectable solution. A study using doramectin injectable solution also demonstrated safety in neonatal calves treated with up to 3 times the recommended dose. In breeding animals (bulls, and cows during folliculogenesis, organogenesis, implantation, and through gestation), a dose 3 times the recommended dose of doramectin injectable solution had no effect on breeding performance. A pharmacokinetic study demonstrated that systemic exposure to doramectin from doramectin topical solution was less than systemic exposure to doramectin from doramectin injectable solution.

PRODUCT INDICATIONS:

DectoGard Pour-On solution is indicated for the treatment and control of the following species of gastrointestinal roundworms, lungworms, eyeworms, grubs (see PRECAUTIONS), biting and sucking lice, horn flies, and mange mites in cattle. Consult your veterinarian for assistance in the diagnosis, treatment, and control of parasitism.

Gastrointestinal roundworms
Ostertagia ostertagi (adults and L4, including inhibited larvae)
O. lyrata (adults)
Haemonchus placei (adults and L4)
Trichostrongylus axei (adults and L4)
T. colubriformis (adults and L4)
Cooperia oncophora (adults [Efficacy below 90% was observed against adult C. oncophora in some clinical studies.] and L4)
C. pectinata (adults)
C. punctata (adults and L4)
C. surnabada (adults)
Bunostomum phlebotomum (adults)
Oesophagostomum radiatum (adults and L4)
Trichuris spp. (adults)

Lungworms (adults and fourth stage larvae)

Dictyocaulus viviparus

Eyeworms | Grubs
Thelazia gulosa (adults) | Hypoderma bovis
T. skrjabini (adults) | H. lineatum
Lice | Horn Flies
Biting Lice | Haematobia irritans
Bovicola (Damalinia) bovis | Mange Mites
Sucking Lice | Chorioptes bovis
Haematopinus eurysternus | Sarcoptes scabiei
Linognathus vituli
Solenopotes capillatus

Doramectin topical solution has been proved to effectively control infections and to protect cattle from reinfection with Cooperia oncophora, Dictyocaulus viviparus, Ostertagia ostertagi, and Oesophagostomum radiatum for 28 days; and Cooperia punctata and Haemonchus placei for 35 days after treatment.

Doramectin topical solution has been proved to effectively control infestations and to protect cattle from reinfestation with Bovicola (Damalinia) bovis for 77 days and Linognathus vituli for 42 days after treatment.

Management Considerations for Horn Flies

DectoGard Pour-On solution provides 7 days of persistent activity against horn flies. The product should be used as part of an integrated control program and be combined with other methods for extended horn fly control. For optimal horn fly control, consult with your veterinarian or a livestock entomologist.

DOSAGE:

Administer DectoGard Pour-On solution to cattle topically at a dosage of 500 mcg doramectin per kg (227 mcg/lb) of body weight. Each mL contains 5 mg of doramectin, sufficient to treat 22 lb (10 kg) of body weight.

For the best results, DectoGard Pour-On solution should be a part of a parasite control program for both internal and external parasites based on the epidemiology of these parasites. Consult a veterinarian or an entomologist for information regarding the most effective timing of applications.

Do not underdose. Ensure each animal receives a complete dose based on a current body weight. Underdosing may result in ineffective treatment, and encourage the development of parasite resistance.

ADMINISTRATION:

DectoGard Pour-On solution should be applied topically along the mid-line of the back in a narrow strip between the withers and tailhead.

Applicators (1-L, 2.5-L and 5-L bottles)

Applicators are available for use with DectoGard Pour-On solution supplied in 1-, 2.5- and 5-L bottles. Directions for use with compatible applicators are provided below. Some applicators may be incompatible with this formulation.

1) Replace the shipping cap on 1-, 2.5- or 5-L backpack with the draw-off cap provided and tighten firmly.

2) Thread the draw-off tubing through the anti-kink spring. Attach the tube to the draw-off cap. Screw the spring counter clockwise over the tubing and draw-off spigot.

3) Invert the bottle.

4) Set the dose to maximum (50 mL). Gently prime the applicator, checking for leaks.

5) Follow the dosing applicator manufacturer's directions to set the required dose and administer.

6) To disconnect the system, proceed as follows:

a) Set backpack in upward position.

b) Discharge residual material from the applicator and draw-off tubing into a separate, clean, dry receptacle.

7) Follow the manufacturer's recommendation for care and maintenance of the dosing applicator.

8) Remove the draw-off cap. Replace with the original cap and tighten firmly.

WARNING:

Flammable! Keep away from heat, sparks, open flame, and other sources of ignition. Not for human use. Keep out of reach of children. The Safety Data Sheet (SDS) contains more detailed occupational safety information. To report adverse effects in users, to obtain more information, or to obtain an SDS, call 1-888-215-1256.
DectoGard Pour-On solution for cattle may be irritating to human skin and eyes, and users should be careful not to apply it to themselves or to other persons. Operators should wear protective clothing including a long-sleeved shirt, protective gloves, and boots with a waterproof coat when applying the product. Protective clothing should be washed after use. If accidental skin contact occurs, wash the affected area immediately with soap and water. If accidental eye exposure occurs, flush the eyes immediately with water and get medical attention.

OTHER WARNINGS:

Parasite resistance may develop to any dewormer, and has been reported for most classes of dewormers. Treatment with a dewormer used in conjunction with parasite management practices appropriate to the geographic area and the animal(s) to be treated may slow the development of parasite resistance. Fecal examinations or other diagnostic tests and parasite management history should be used to determine if the product is appropriate for the herd prior to the use of any dewormer. Following the use of any dewormer, effectiveness of treatment should be monitored (for example, with the use of a fecal egg count reduction test or another appropriate method). A decrease in a drug’s effectiveness over time as calculated by fecal egg count reduction tests may indicate the development of resistance to the dewormer administered. Your parasite management plan should be adjusted accordingly based on regular monitoring.

RESIDUE WARNING:

Cattle must not be slaughtered for human consumption within 45 days of treatment. Not for use in female dairy cattle 20 months of age or older. A withdrawal period has not been established for this product in preruminating calves. Do not use in calves to be processed for veal.

PRECAUTIONS:

DectoGard Pour-On solution has been developed specifically for use in cattle only. This product should not be used in other animal species as severe adverse reactions, including fatalities in dogs, may result.

This product is to be applied to skin surface only. Do not administer orally or parenterally.

Do not apply to areas of skin which are caked with mud or manure.

Wash hands after use.

Do not smoke or eat while handling the product.

Cloudiness in the formulation may occur when DectoGard Pour-On solution is stored at temperatures below 0°C (32°F). Allowing to warm to room temperature will restore the normal appearance without affecting efficacy.

DectoGard Pour-On solution is highly effective against cattle grubs. However, proper timing of treatment is important. For most effective results, cattle should be treated as soon as possible after the end of the heel fly (warble) season.

Destruction of Hypoderma larvae (cattle grubs) at the period when these grubs are in vital areas may cause undesirable host-parasite reactions including the possibility of fatalities. Killing H. lineatum when it is in the tissue surrounding the gullet may cause bloat; killing H. bovis when it is in the vertebral canal may cause staggering or paralysis. These reactions are not specific to treatment with DectoGard Pour-On solution, but can occur with any successful treatment of grubs. Cattle should be treated either before or after the migratory phase of grub development. Consult your veterinarian concerning the proper time for treatment.

Cattle treated with DectoGard Pour-On solution after the end of heel fly season may be re-treated with DectoGard Pour-On during the winter for internal parasites, mange mites, or biting and sucking lice, without danger of grub-related reactions. A planned parasite control program is recommended.

USE CONDITIONS:

Varying weather conditions, including rainfall, do not affect the efficacy of DectoGardPour-On.

ENVIRONMENTAL SAFETY:

Studies indicate that when doramectin comes in contact with the soil, it readily and tightly binds to the soil and becomes inactive over time. Free doramectin may adversely affect fish and certain aquatic organisms. Do not permit cattle to enter lakes, streams or ponds for at least 6 hours after treatment. Do not contaminate water by direct application or by the improper disposal of drug containers. Dispose of containers in an approved landfill or by incineration. As with other avermectins, doramectin is excreted in the dung of treated animals and can inhibit the reproduction and growth of pest and beneficial insects that use dung as a source of food and for reproduction. The magnitude and duration of such effects are species and life-cycle specific. When used according to label directions, the product is not expected to have an adverse impact on populations of dung-dependent insects.

STORAGE AND HANDLING

Store Below 30°C (86°F)

Protect From Light

HOW SUPPLIED:

DectoGard Pour-On solution is available in 1-L, 2.5-L, and 5-L multi-dose containers.

Approved by FDA under ANADA # 200-738
Consult your veterinarian for assistance in the diagnosis, treatment, and control of parasitism.
Not for human use.
Restricted Drug (CA) Use only as directed.
Manufactured by:

Aurora Pharmaceutical, Inc.

Northfield, MN 55057

PRINCIPAL DISPLAY PANEL - 5 L Bottle front and back

IN 50-1739

rev 05/2022

IN 50-1741

rev 06/2025

PRINCIPAL DISPLAY PANEL - 5 L Carton

IN 40-1744

rev 11/2022